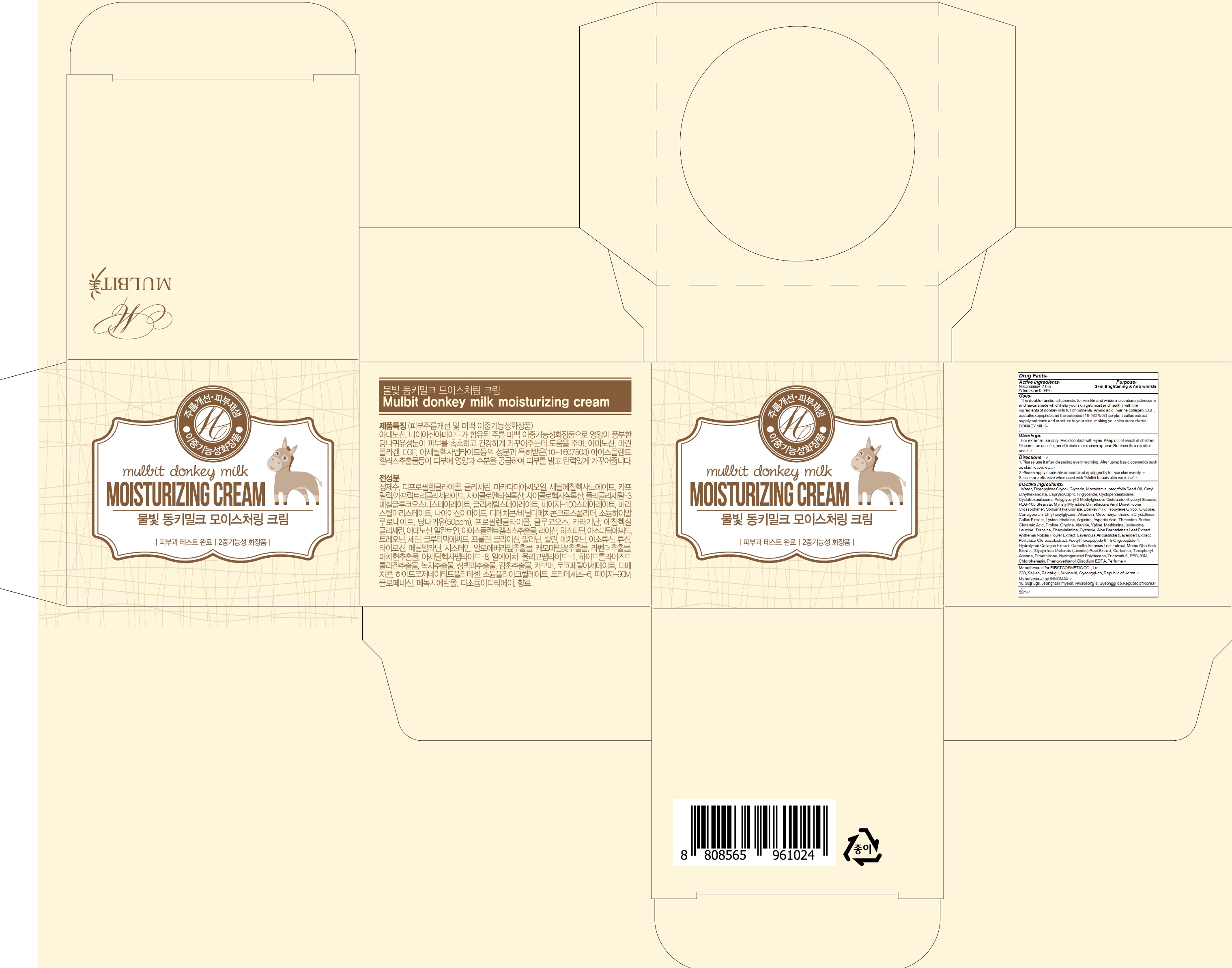 DRUG LABEL: MULBIT Donkey Milk Moisturizing
NDC: 71635-040 | Form: CREAM
Manufacturer: First Cosmetic Co., Ltd
Category: otc | Type: HUMAN OTC DRUG LABEL
Date: 20171020

ACTIVE INGREDIENTS: Niacinamide 1.0 g/50 mL; Adenosine 0.02 g/50 mL
INACTIVE INGREDIENTS: Water; Dipropylene Glycol

ACTIVE INGREDIENT

Active ingredients: Niacinamide 2.0%, Adenosine 0.04%

INACTIVE INGREDIENT

Inactive ingredients: Water, Dipropylene Glycol, Glycerin, Macadamia Integrifolia Seed Oil, Cetyl Ethylhexanoate, Caprylic/Capric Triglyceride, Cyclopentasiloxane, Cyclohexasiloxane, Polyglyceryl-3 Methylglucose Distearate, Glyceryl Stearate, PEG-100 Stearate, Myristyl Myristate, Dimethicone/Vinyl Dimethicone Crosspolymer, Sodium Hyaluronate, Donkey milk, Propylene Glycol, Glucose, Carrageenan, Ethylhexylglycerin, Allantoin, Mesembryanthemum Crystallinum Callus Extract, Lysine, Histidine, Arginine, Aspartic Acid, Threonine, Serine, Glutamic Acid, Proline, Glycine, Alanine, Valine, Methionine, Isoleucine, Leucine, Tyrosine, Phenylalanine, Cysteine, Aloe Barbadensis Leaf Extract, Anthemis Nobilis Flower Extract, Lavandula Angustifolia (Lavender) Extract, Portulaca Oleracea Extract, Acetyl Hexapeptide-8, rh-Oligopeptide-1, Hydrolyzed Collagen Extract, Camellia Sinensis Leaf Extract, Morus Alba Bark Extract, Glycyrrhiza Uralensis (Licorice) Root Extract, Carbomer, Tocopheryl Acetate, Dimethicone, Hydrogenated Polydecene, Trideceth-6, PEG-90M, Chlorphenesin, Phenoxyethanol, Disodium EDTA, Perfume

PURPOSE

Purpose: Skin Brightening & Anti wrinkle

WARNINGS

Warnings: For external use only. Avoid contact with eyes. Keep out of reach of children. Discontinue use if signs of irritation or rashes appear. Replace the cap after use it.

KEEP OUT OF REACH OF CHILDREN

Uses

Uses: The double-functional cosmetic for wrinkle and whitening contains adenosine and niacinamide which help your skin get moist and healthy with the ingredients of donkey milk full of nutrients. Amino acid, marine collagen, EGF, acetalhexapeptide and the patented (10-1607503) ice plant callus extract supply nutrients and moisture to your skin, making your skin more elastic. DONKEY MILK

Directions

Directions: 1.Please use it after cleansing every morning. After using basic cosmetics such as skin, lotion, etc., 2.Please apply moderate amount and apply gently to face skin evenly. 3.It is more effective when used with "Mulbit beauty skin care line".